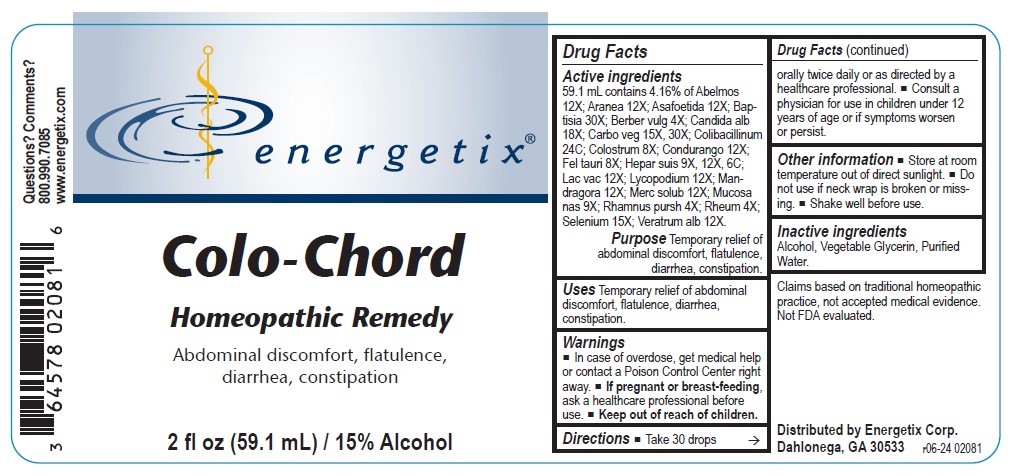 DRUG LABEL: Colo-Chord
NDC: 64578-0061 | Form: LIQUID
Manufacturer: Energetix Corporation
Category: homeopathic | Type: HUMAN OTC DRUG LABEL
Date: 20241211

ACTIVE INGREDIENTS: ABELMOSCHUS MOSCHATUS SEED 12 [hp_X]/59.1 mL; ARANEUS DIADEMATUS 12 [hp_X]/59.1 mL; ASAFETIDA 12 [hp_X]/59.1 mL; BAPTISIA TINCTORIA ROOT 30 [hp_X]/59.1 mL; BERBERIS VULGARIS ROOT BARK 4 [hp_X]/59.1 mL; CANDIDA ALBICANS 18 [hp_X]/59.1 mL; ACTIVATED CHARCOAL 15 [hp_X]/59.1 mL; ESCHERICHIA COLI 24 [hp_C]/59.1 mL; BOS TAURUS COLOSTRUM 8 [hp_X]/59.1 mL; MARSDENIA CONDURANGO BARK 12 [hp_X]/59.1 mL; BOS TAURUS BILE 8 [hp_X]/59.1 mL; PORK LIVER 9 [hp_X]/59.1 mL; COW MILK 12 [hp_X]/59.1 mL; LYCOPODIUM CLAVATUM SPORE 12 [hp_X]/59.1 mL; MANDRAGORA OFFICINARUM ROOT 12 [hp_X]/59.1 mL; MERCURIUS SOLUBILIS 12 [hp_X]/59.1 mL; SUS SCROFA NASAL MUCOSA 9 [hp_X]/59.1 mL; FRANGULA PURSHIANA BARK 4 [hp_X]/59.1 mL; RHEUM OFFICINALE ROOT 4 [hp_X]/59.1 mL; SELENIUM 15 [hp_X]/59.1 mL; VERATRUM ALBUM ROOT 12 [hp_X]/59.1 mL
INACTIVE INGREDIENTS: WATER; GLYCERIN; ALCOHOL

Colo-Chord

ACTIVE INGREDIENT

Active ingredients59.1 mL contains 4.16% of Abelmos 12X; Aranea 12X; Asafoetida 12X; Baptisia 30X; Berber vulg 4X; Candida alb 18X;
Carbo veg 15X, 30X; Colibacillinum 24C; Colostrum 8X; Condurango 12X; Fel tauri 8X; Hepar suis 9X, 12X, 6C; Lac vac 12X; Lycopodium 12X;
Mandragora 12X; Merc solub 12X; Mucosa nas 9X; Rhamnus pursh 4X; Rheum 4X; Selenium 15X; Veratrum alb 12X.

Claims based on traditional homeopathic practice, not accepted medical evidence. Not FDA evaluated.

Uses

Temporary relief of abdominal discomfort, flatulence, diarrhea, constipation.

Warnings

- In case of overdose, get medical help or contact a Poison Control Center right away.
- If pregnant or breast feeding, ask a health professional before use.

Keep out of reach of children.

Directions

- Take 30 drops orally twice daily or as directed by a healthcare professional.
- Consult a physician for use in children under 12 years of age or if symptoms worsen or persist.

Other information

- Store at room temperature out of direct sunlight.
- Do not use if neck wrap is broken or missing.
- Shake well before use.

Inactive ingredients

Alcohol, Vegetable Glycerin, Purified Water.

QUESTIONS

Distributed by Energetix Corp.

Dahlonega, GA 30533

Questions? Comments?

800.990.7085

www.energetix.com

PACKAGE LABEL

energetix®

Colo-Chord

Homeopathic Remedy

Abdominal discomfort, flatulence, diarrhea, constipation.

2 fl oz (59.1 mL) / 15% Alcohol

PURPOSE

PurposeTemporary relief of abdominal discomfort, flatulence, diarrhea, constipation.